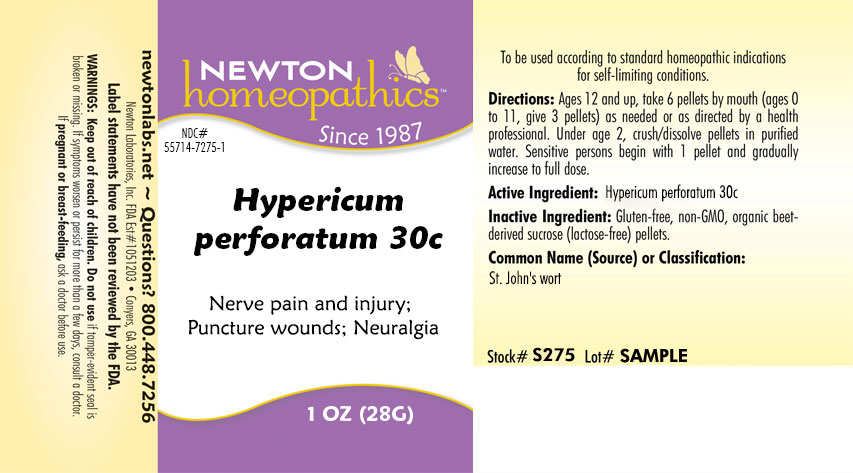 DRUG LABEL: Hypericum perforatum
NDC: 55714-7275 | Form: PELLET
Manufacturer: Newton Laboratories, Inc.
Category: homeopathic | Type: HUMAN OTC DRUG LABEL
Date: 20201218

ACTIVE INGREDIENTS: HYPERICUM PERFORATUM 15 [hp_X]/1 g
INACTIVE INGREDIENTS: SUCROSE

Hypericum 7275P

INDICATIONS & USAGE SECTION

Nerve pain and injury, Puncture wounds, Neuralgia.

DOSAGE & ADMINISTRATION SECTION

Directions: Ages 12 and up, take 6 pellets by mouth (ages 0 to 11, give 3 pellets) as needed or as directed by a health professional. Under age 2, crush/dissolve pellets in purified water. Sensitive persons begin with 1 pellet and gradually increase to full dose.

OTC - ACTIVE INGREDIENT SECTION

Hypericum perforatum 15x, 10x, 200c, 30c.

OTC - PURPOSE SECTION

Nerve pain and injury, Puncture wounds, Neuralgia.

INACTIVE INGREDIENT SECTION

Inactive Ingredients: Gluten-free, non-GMO, organic beet-derived sucrose (lactose free) pellets.

QUESTIONS SECTION

newtonlabs.net - Questions? 1.800.448.7256

Newton Laboratories, Inc. FDA Est # 1051203 - Conyers, GA 30013

WARNINGS SECTION

WARNINGS: Keep out of reach of children. Do not use if tamper-evident seal is broken or missing. If symptoms worsen or persist for more than a few days, consult a doctor. If pregnant or breast-feeding, ask a doctor before use.

OTC - PREGNANCY OR BREAST FEEDING SECTION

If pregnant or breast-feeding, ask a doctor before use.

OTC - KEEP OUT OF REACH OF CHILDREN SECTION

Keep out of reach of children.